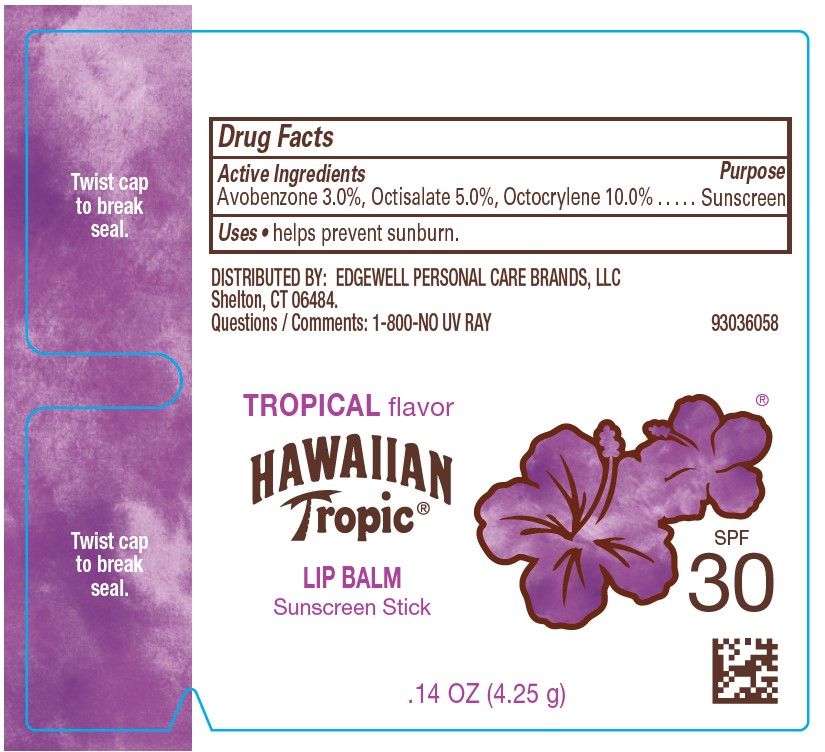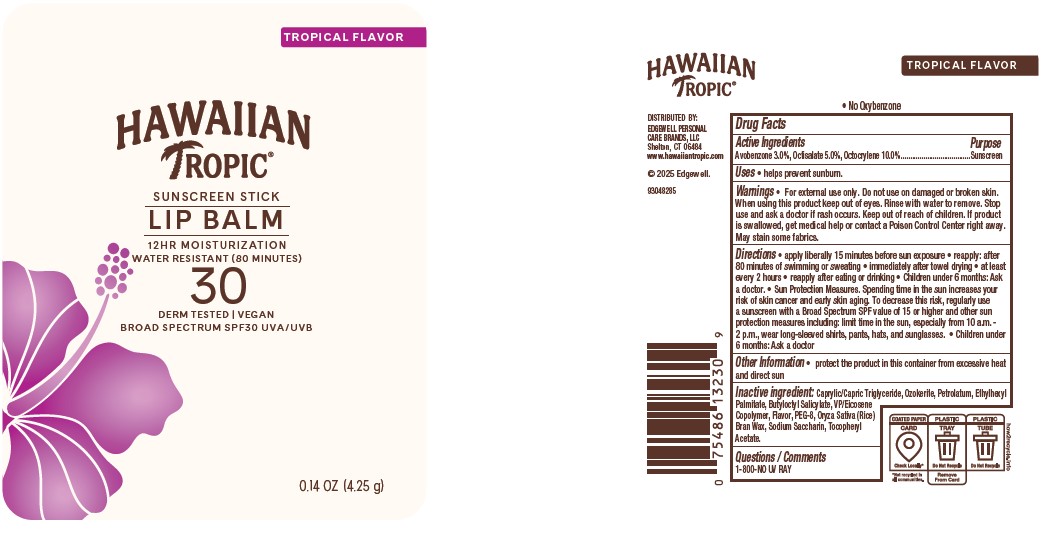 DRUG LABEL: Hawaiian Tropic Lip Balm Sunscreen SPF 30
NDC: 63354-520 | Form: STICK
Manufacturer: Edgewell Personal Care Brands LLC
Category: otc | Type: HUMAN OTC DRUG LABEL
Date: 20260106

ACTIVE INGREDIENTS: OCTOCRYLENE 10 g/100 g; OCTISALATE 5 g/100 g; AVOBENZONE 3 g/100 g
INACTIVE INGREDIENTS: MEDIUM-CHAIN TRIGLYCERIDES; PETROLATUM; CERESIN; ETHYLHEXYL PALMITATE; VINYLPYRROLIDONE/EICOSENE COPOLYMER; SACCHARIN SODIUM ANHYDROUS; BUTYLOCTYL SALICYLATE; POLYETHYLENE GLYCOL 400; RICE BRAN; .ALPHA.-TOCOPHEROL ACETATE

Active Ingredients

Avobenzone 3.0%, Octisalate 5.0%, Octocrylene 10.0%

Purpose

Sunscreen

Uses

• helps prevent sunburn.

Warnings

• For external use only.

May stain some fabrics.

Do not use

on damaged or broken skin.

When using this product

keep out of eyes. Rinse with water to remove.

Stop use and ask a doctor

if rash occurs.

Keep out of reach of children.

If product is swallowed, get medical help or contact a Poison Control Center right away.

Directions

• apply liberally 15 minutes before sun exposure • reapply: after 80 minutes of swimming or sweating • immediately after towel drying • at least every 2 hours • reapply after eating or drinking • Children under 6 months: Ask a doctor. •Sun Protection Measures. Spending time in the sun increases your risk of skin cancer and early skin aging. To decrease this risk, regularly use a sunscreen with a Broad Spectrum SPF value of 15 or higher and other sun protection measures including: limit time in the sun, especially from 10 a.m. - 2 p.m., wear long-sleeved shirts, pants, hats, and sunglasses. •Children under 6 months: Ask a doctor

Inactive ingredient

Caprylic/Capric Triglyceride, Ozokerite, Petrolatum, Ethylhexyl Palmitate, VP/Eicosene Copolymer, Butyloctyl Salicylate, Flavor, PEG-8, Oryza Sativa (Rice) Bran Wax, Sodium Saccharin, Tocopheryl Acetate.

Other Information

• protect this product from excessive heat and direct sun.

Questions / Comments

1-800-NO UV RAY

Principal Display Panel

TROPICAL FLAVOR

HAWAIIAN TROPIC(R)
SUNSCREEN STICK

LIP BALM

12 HR MOISTURIZATION
WATER RESISTANT (80 minutes)

30

DERM TESTED | VEGAN
BROAD SPECTRUM SPF30 UVA/UVB

0.14 OZ (4.25g)